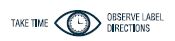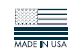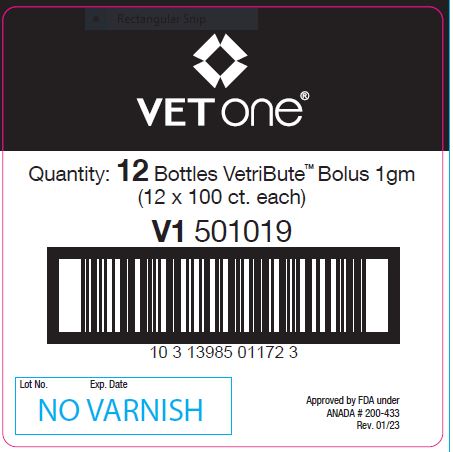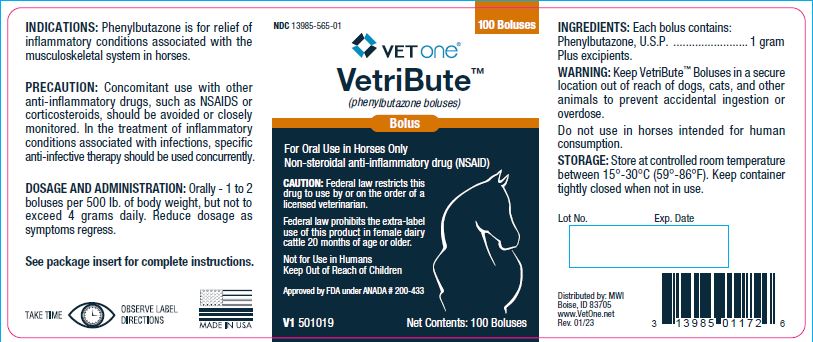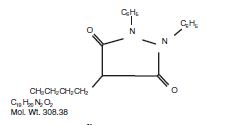 DRUG LABEL: VetriBute
NDC: 13985-565 | Form: TABLET
Manufacturer: MWI
Category: animal | Type: PRESCRIPTION ANIMAL DRUG LABEL
Date: 20250708

ACTIVE INGREDIENTS: PHENYLBUTAZONE 1 g/1 1

VetriBute™
(phenylbutazone boluses)

DESCRIPTION

For Oral Use in Horses Only.

Non-steroidal anti-inflammatory drug (NSAID)

CAUTION:

Federal law restricts this drug to use by or on the order of a licensed veterinarian.
Federal law prohibits the extra-label use of this product in female dairy cattle 20 months of age or older.
Not for Use in Humans
Keep Out of Reach of Children
Approved by FDA under ANADA # 200-433

DESCRIPTION & PHARMACOLOGY:

Phenylbutazone chemically is 4-butyl-1, 2- diphenyl-3, 5-pyrazolidinedione. It has the following structural formula:

Phenylbutazone was first synthesized in 1948 and introduced into human medicine in 1949, Kuzell^1,2,3, Payne^4, Fleming^5, and Denko^6, demonstrated the clinical effectiveness of phenylbutazone in gout, gouty arthritis, acute arthritis, acute rheumatism and various other rheumatoid disorders in humans. Fabre^7, Domenjoz^8, Wilhelmi^9, and Yourish^10, have established the anti-rheumatic and anti-inflammatory activity of phenylbutazone. It is entirely unrelated to the steroid hormones.
Toxicity of phenylbutazone has been investigated in rats and mice^11, Ogilvie and Sutter^12, have also made a study on the chronic toxicity of phenylbutazone in dogs. They have shown that dogs receiving 10 mg. and 100 mg. per Kg. body weight, per day for 90 days, maintain good appetites, excrete normal feces, gain weight and maintain a normal blood picture. They also report no abnormal macroscopic or microscopic changes in sacrificed animals which could have been attributed to the drug.
Phenylbutazone has been used by Camberos^13 in thoroughbred horses. Favorable results were reported in cases of traumatism, muscle rupture, strains and inflammations of the third phalanx. Results were not as favorable in the periodic treatment of osteo-arthritis of medial and distal bones of the hock, arthritis of the stifle and hip, arthrosis of the trapezious muscles, and generalized arthritis. Sutter^14 reported a favorable response in chronic equine arthritis of long duration, fair results in a severely bruised mare, and poor results in two cases where the condition was limited to the third phalanx.

INDICATIONS:

Phenylbutazone is for the relief of inflammatory conditions associated with the musculoskeletal system in horses.

DOSAGE & ADMINISTRATION:

For horses only.
HORSES: Orally - 1 to 2 boluses per 500 lb. body weight. Do not exceed 4 grams daily. Reduce dosage as symptoms regress. Intermittent
treatment given only when symptoms appear may be indicated.

INGREDIENTS:

Each bolus contains:
Phenylbutazone, U.S.P. ............................. 1 gram
Plus excipients.

CONTRAINDICATIONS:

Use with caution in patients who have a history of drug allergy.

PRECAUTION:

Concomitant use with other antiinflammatory drugs, such as NSAIDS or corticosteroids, should be avoided or closely monitored. In the treatment of inflammatory conditions associated with infections, specific anti-infective therapy should be used concurrently.

WARNING:

Not for use in humans. Keep out of reach of children.

Keep Phenylbutazone Boluses in a secure location out of reach of dogs, cats, and other animals to prevent accidental ingestion or overdose.

Do not use in horses intended for human consumption.

CONTACT INFORMATION:

To report suspected adverse events, for technical assistance or to obtain a copy of the Safety Data Sheet (SDS), contact First Priority, Inc. at (800) 650-4899 or www.prioritycare.com. For additional information about adverse drug experience reporting for animal drugs, contact FDA at 1-888-FDA-VETS or http://www.fda.gov/reportanimalae

CAUTION:

Federal law restricts this drug to use by or on the order of a licensed veterinarian. Federal law prohibits the extra-label use of this
product in female dairy cattle 20 months of age or older.

AVAILABILITY:

Available in 1 gm. boluses - 100 boluses per bottle.

STORAGE:

Store at controlled room temperature between 15°-30°C (59°-86°F). Keep container tightly closed when not in use.

Lot No. Exp. Date

REFERENCES

1. Kuzell, W.C., Schafferzick, R.W., Naughler, W.E., Gandia, G. and Mankle, E.A.: A.M.A. Arch. Inst. Med., 92; 646 (1953).
2. Kuzell, W.C., Schafferzick, R.W., Brown, B. and Mankle, E.A.: J.A.M.A. 149; 729 (1952).
3. Kuzell, W.C., and Schafferzick, R.W.: Calif. Med. 77; 319 (1952).
4. Payne, R.W., Shelter, M.R., Farr, C.H., Hellbaum, A.A. and Ishmall, W.K.: J. Lab. Clin. Med., 45; 331 (1955).
5. Fleming, J., and Will, G.: Ann. Rheumat. Dist., 12; 95 (1953).
6. Denko, C.W., and Rumi, D.: American Pract. 6; 1865 (1956).
7. Fabre, J., et al: Semain. Hop. (Paris) 31; 87 (1955).
8. Domenjoz, R., et al: Arzneimittel-Forsch, 5; 488 (1955).
9. Wilhelmi, G. and Pulver, R.: Arzneimittel- Forsch, 5; 221 (1955).
10. Yourish, W., Paton, B., Brodie, B., Burns, J.: A.M.A. Arch. Ophth., 53; 264 (1955).
11. Hazelton, L.W., Tusing, T.W. and Hollana, E.G.: J. Pharmacol. Exper. Ther., 109; 387 (1953).
12. Ogilvie, F.B. and Sutter, M.D.: Vet. Med. 52; 492-4 (1957).
13. Camberos, H.R.: Rev. Med. Vet. (Buenos Aires) 38; 9 (1956).
14. Sutter, M.D.: Vet. Med., 53; 83 (Feb. 1958).

INFORMATION FOR OWNERS/CAREGIVERS

Distributed by: MWI
Boise, ID 83705
www.VetOne.net
Rev. 01/23